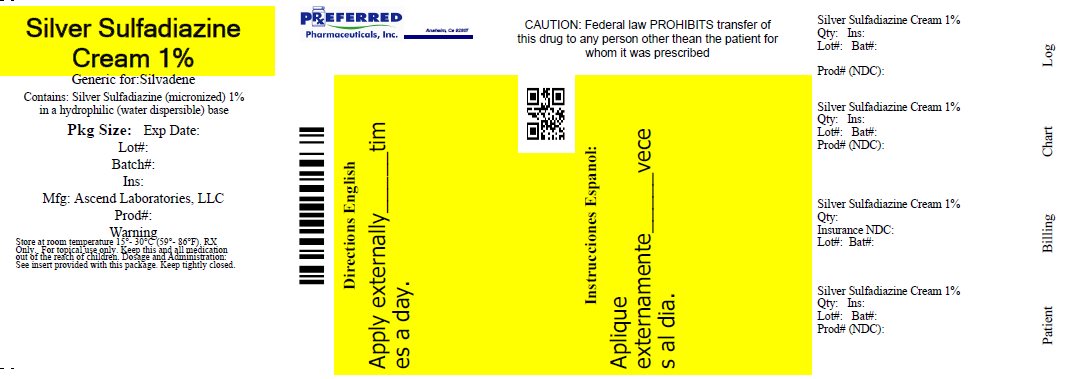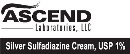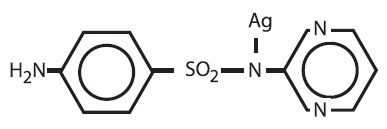 DRUG LABEL: Thermazene
NDC: 68788-0600 | Form: CREAM
Manufacturer: Preferred Pharmaceuticals, Inc.
Category: prescription | Type: HUMAN PRESCRIPTION DRUG LABEL
Date: 20260216

ACTIVE INGREDIENTS: Silver Sulfadiazine 10 mg/1 g
INACTIVE INGREDIENTS: Water; Stearyl Alcohol; Petrolatum; POLYOXYL 40 STEARATE TYPE I; Propylene Glycol; Isopropyl Myristate; Sorbitan Monooleate; Methylparaben 0.3 mg/1 g

DESCRIPTION

Silver sulfadiazine cream, USP 1% is a soft, white, water dispersible cream containing the antimicrobial agent silver sulfadiazine in micronized form for topical application. Each gram of silver sulfadiazine cream contains 10mg of micronized silver sulfadiazine.
This active agent has the following structural formula:

Silver sulfadiazine cream contains 1% w/w silver sulfadiazine. The vehicle in which the active ingredient is dispersed consists of water, stearyl alcohol, white petrolatum, polyoxyl 40 stearate, propylene glycol, isopropyl myristate, and sorbitan monooleate with 0.3% methylparaben as a preservative.

CLINICAL PHARMACOLOGY

Silver sulfadiazine has broad antimicrobial activity. It is bactericidal for many gram-negative and gram-positive bacteria as well as being effective against yeast. Results from in vitro testing are listed below. Sufficient data have been obtained to demonstrate that silver sulfadiazine will inhibit bacteria that are resistant to other antimicrobial agents and that the compound is superior to sulfadiazine. Studies utilizing radioactive micronized silver sulfadiazine, electron microscopy, and biochemical techniques have revealed that the mechanism of action of silver sulfadiazine on bacteria differs from silver nitrate and sodium sulfadiazine. Silver sulfadiazine acts only on the cell wall to produce its bactericidal effect.

Results of In Vitro Testing With Silver Sulfadiazine Cream, 1% Concentration of Silver Sulfadiazine
Number of Sensitive Strains / Total Number of Strains Tested

Genus and Species 50 micrograms/mL 100 micrograms/mL

Xanthomonas (Pseudomonas)

Maltophilia 7/7 7/7

Enterobacter Species 48/50 50/50

Enterobacter cloacae 24/24 24/24

Klebsiella Species 53/54 54/54

Escherichia Coli 63/63 63/63

Serratia Species 27/28 28/28

Proteus Mirabilis 53/53 53/53

Morganella Morganii 10/10 10/10

Providencia Rettgeri 2/2 2/2

Proteus Vulgaris 2/2 2/2

Providencia Species 1/1 1/1

Citrobacter Species 10/10 10/10

Acinetobacter Calcoaceticus 10/11 11/11

Clostridium Perfringens 0/2 2/2

Clostridium Perfringens 0/2 2/2

Candida Albicans 43/50 50/50

Silver sulfadiazine is not a carbonic anhydrase inhibitor and may be useful in situations where such agents are contraindicated.

INDICATIONS AND USAGE

Silver sulfadiazine cream, USP 1% is a topical antimicrobial drug indicated as an adjunct for the prevention and treatment of wound sepsis in patients with second and third degree burns.

CONTRAINDICATIONS

Silver sulfadiazine cream, USP 1% is contraindicated in patients who are hypersensitive to silver sulfadiazine or any of the other ingredients in the preparation.
Because sulfonamide therapy is known to increase the possibility of kernicterus, silver sulfadiazine cream, USP 1% should not be used on pregnant women approaching or at term, on premature infants, or on newborn infants during the first 2 months of life.

WARNINGS

Absorption of silver sulfadiazine varies depending upon the percent of body surface area and the extent of the tissue damage. Although few have been reported, it is possible that any adverse reaction associated with sulfonamides may occur. Some of the reactions which have been associated with sulfonamides are as follows: blood dyscrasias including agranulocytosis, aplastic anemia, thrombocytopenia, leukopenia, and hemolytic anemia; dermatologic and allergic reactions, including life-threatening cutaneous reactions [Stevens-Johnson syndrome (SJS), toxic epidermal necrolysis (TEN) and exfoliative dermatitis]; gastrointestinal reactions, hepatitis and hepatocellular necrosis; CNS reactions; and toxic nephrosis.
There is a potential cross-sensitivity between silver sulfadiazine and other sulfonamides. If allergic reactions attributable to treatment with silver sulfadiazine occur, continuation of therapy must be weighed against the potential hazards of the particular allergic reaction.
Fungal proliferation in and below the eschar may occur. However, the incidence of clinically reported fungal superinfection is low.
The use of silver sulfadiazine cream, USP 1% in some cases of glucose-6-phosphate dehydrogenase-deficient individuals may be hazardous, as hemolysis may occur.

PRECAUTIONS

General. If hepatic and renal functions become impaired and elimination of the drug decreases accumulation may occur. Discontinuation of silver sulfadiazine cream, USP 1% should be weighed against the therapeutic benefit being achieved.
In considering the use of topical proteolytic enzymes in conjunction with Silver sulfadiazine cream, USP 1% the possibility should be noted that silver may inactivate such enzymes.
Laboratory Tests. In the treatment of burn wounds involving extensive areas of the body, the serum sulfa concentrations may approach adult therapeutic levels (8 to 12mg %). Therefore, in these patients it would be advisable to monitor serum sulfa concentrations. Renal function should be carefully monitored and the urine should be checked for sulfa crystals.
Absorption of the propylene glycol vehicle has been reported to affect serum osmolality, which may affect the interpretation of laboratory tests.

CARCINOGENESIS AND MUTAGENESIS AND IMPAIRMENT OF FERTILITY

Carcinogenesis, Mutagenesis, Impairment of Fertility. Long-term dermal toxicity studies of 24 months duration in rats and 18 months in mice with concentrations of silver sulfadiazine three to ten times the concentration in silver sulfadiazine cream, USP 1% revealed no evidence of carcinogenicity.

PREGNANCY: TERATOGENIC EFFECTS:

Pregnancy Category B. A reproductive study has been performed in rabbits at doses up to three to ten times the concentration of silver sulfadiazine in silver sulfadiazine cream, USP 1% and has revealed no evidence of harm to the fetus due to silver sulfadiazine. There are, however, no adequate and well-controlled studies in pregnant women. Because animal reproduction studies are not always predictive of human response, this drug should be used during pregnancy only if clearly justified, especially in pregnant women approaching or at term. (See)

NURSING MOTHERS

Nursing Mothers. It is not known whether silver sulfadiazine cream, USP 1% is excreted in human milk. However, sulfonamides are known to be excreted in human milk and all sulfonamides derivatives are known to increase the possibility of kernicterus. Because of the possibility for serious adverse reactions in nursing infants from sulfonamides, a decision should be made whether to discontinue nursing or to discontinue the drug, taking into account the importance of the drug to the mother.

GERIATRIC USE

Geriatric Use. Of the total number of subjects in clinical studies of silver sulfadiazine cream, USP 1% seven percent were 65 years of age and over. No overall differences in safety or effectiveness were observed between these subjects and younger subjects, and other reported clinical experience has not identified differences in responses between the elderly and younger patients, but greater sensitivity of some older individuals cannot be ruled out.

PEDIATRIC USE

Pediatric Use. Safety and effectiveness in children have not been established. (See)

ADVERSE REACTIONS

Several cases of transient leukopenia have been reported in patients receiving silver sulfadiazine therapy.^1,2,3 Leukopenia associated with silver sulfadiazine administration is primarily characterized by decreased neutrophil count. Maximal white blood cell depression occurs within two to four days of initiation of therapy. Rebound to normal leukocyte levels follows onset within two to three days. Recovery is not influenced by continuation of silver sulfadiazine therapy. An increased incidence has been seen in patients treated concurrently with cimetidine.
Other infrequently occurring events include skin necrosis, erythema multiforme, skin discoloration, burning sensation, rashes, and interstitial nephritis.
Reduction in bacterial growth after application of topical antibacterial agents has been reported to permit spontaneous healing of deep partial-thickness burns by preventing conversion of the partial thickness to full thickness by sepsis. However, reduction in bacterial colonization has caused delayed separation, in some cases necessitating escharotomy in order to prevent contracture.

DOSAGE AND ADMINISTRATION

Prompt institution of appropriate regimens for care of the burned patient is of prime importance and includes the control of shock and pain. The burn wounds are then cleansed and debrided; silver sulfadiazine cream, USP 1% is then applied under sterile conditions. The burn areas should be covered with silver sulfadiazine cream, USP 1% at all times. The cream should be applied once to twice daily to a thickness of approximately one sixteenth of an inch. Whenever necessary, the cream should be reapplied to any areas from which it has been removed by patient activity. Administration may be accomplished in minimal time because dressings are not required. However, if individual patient requirements make dressings necessary, they may be used.
Reapply immediately after hydrotherapy. Treatment with silver sulfadiazine cream, USP 1% should be continued until satisfactory healing has occurred or until the burn site is ready for grafting. The drug should not be withdrawn from the therapeutic regimen while there remains the possibility of infection except if a significant adverse reaction occurs.

REFERENCES

1. Caffee F, Bingham H. Leukopenia and silver sulfadiazine. J Trauma. 1982;22: 586–587.
2. Jarret F, Ellerbe S, Demling R. Acute leukopenia during topical burn therapy with silver sulfadiazine. Amer J Surg. 1978;135: 818–819.
3. Kiker RG, Carvajal HF, Micak RP, Larson DL. A controlled study of the effects of silver sulfadiazine on white blood cell counts in burned children. J Trauma. 1977;17: 835–836.

How Supplied

Silver sulfadiazine cream, USP 1% - white to off-white cream

50 Gram jar - 68788-0600-5

25 Gram Tube – 68788-0600-2

PACKAGE LABEL

———PRINCIPAL DISPLAY PANEL———

Silver sulfadiazine (micronized) 1% in a hydrophilic (water dispersible) base consisting of water, stearyl alcohol, white petrolatum, polyoxyl 40 stearate, propylene glycol, isopropyl myristate, sorbitan monooleate, with 0.3% methylparaben as a preservative.

DOSAGE AND ADMINISTRATION: See insert provided with this package.
WARNING: KEEP OUT OF REACH OF CHILDREN.
STORE AT ROOM TEMPERATURE 15°-30°C (59° - 86°F).
For Topical Use Only. Keep tube tightly closed. See Crimp for Control Number/Expiration Date.

Mfd. for: Ascend Laboratories, LLC Parsippany, NJ 07054
Mfd. by: Crown Laboratories, Inc. Johnson City, TN 37604
Product information: 1-877-272-7901 P1837.03
NDC 68788-0600-4
ASCEND Laboratories, LLC
Silver Sulfadiazine Cream, USP 1% Rx ONLY Net Wt. 25 g

Relabeled By: Preferred Pharmaceuticals Inc.